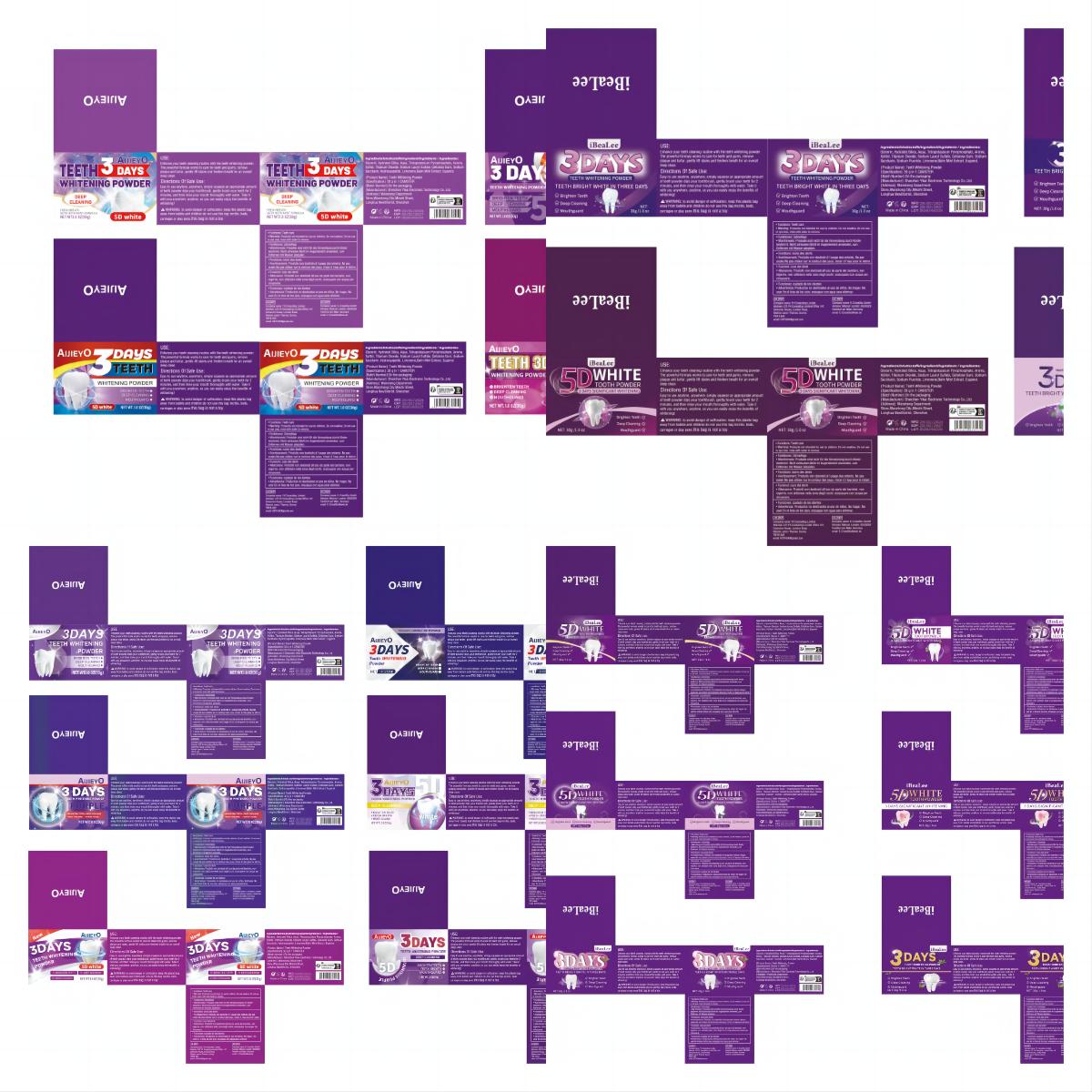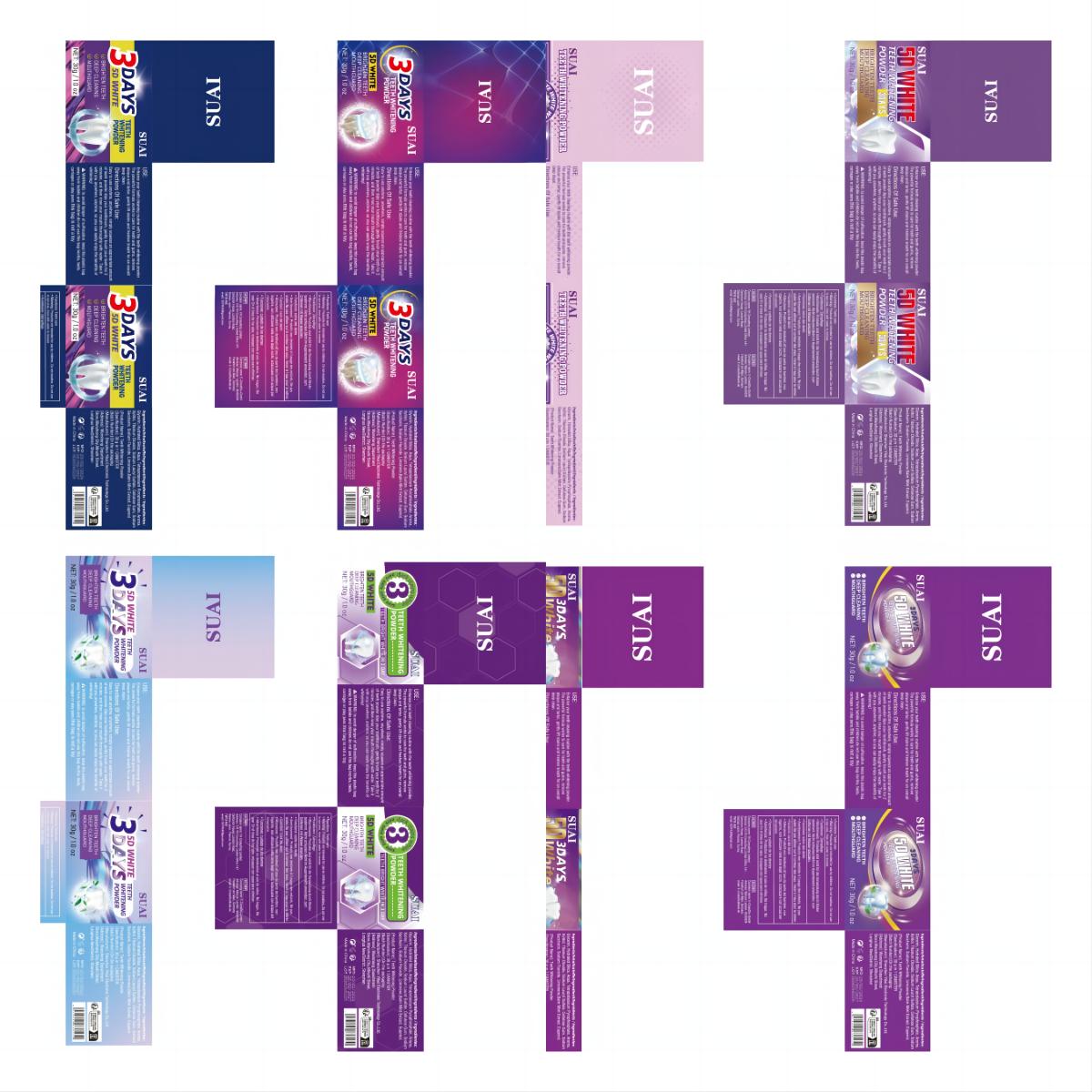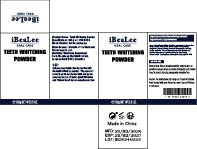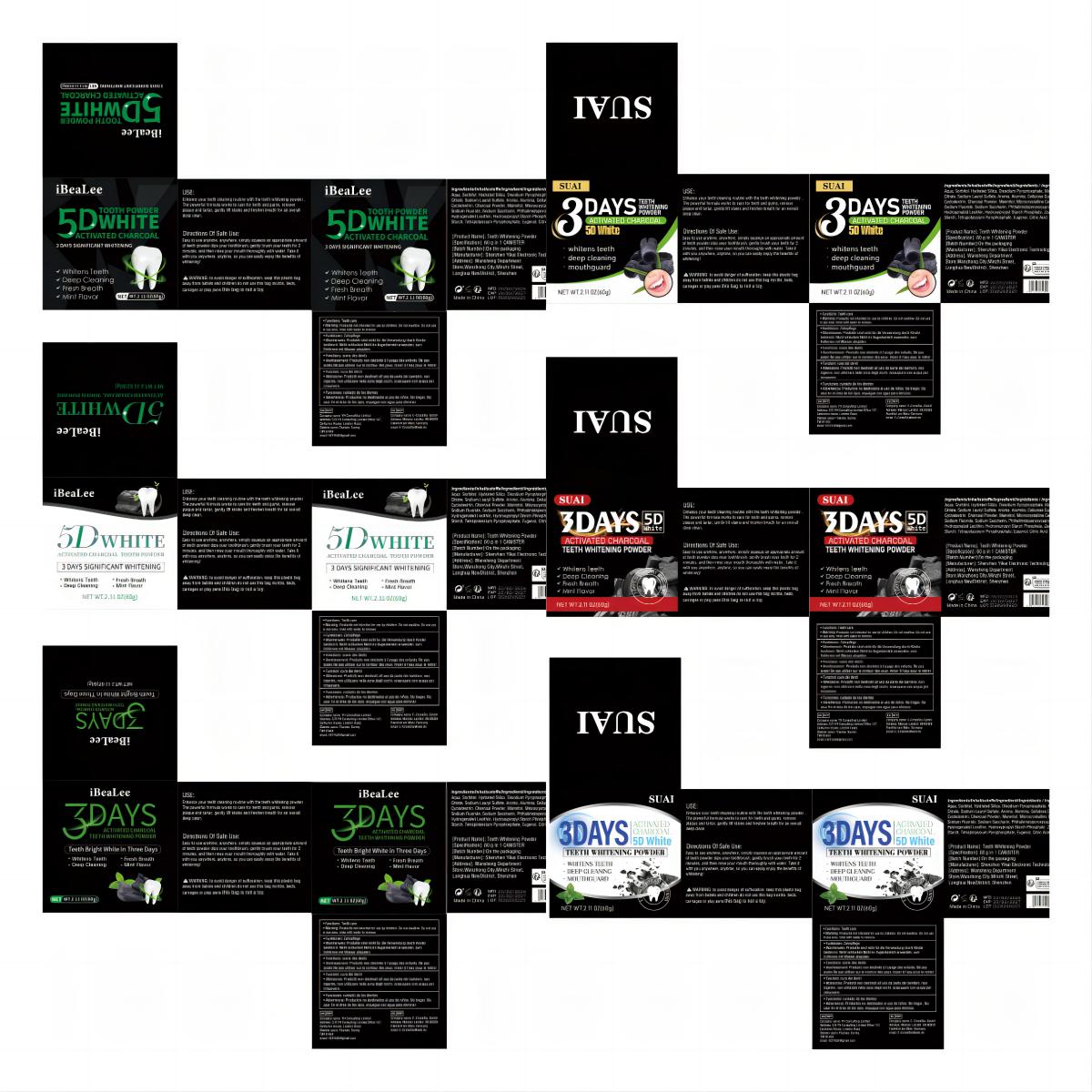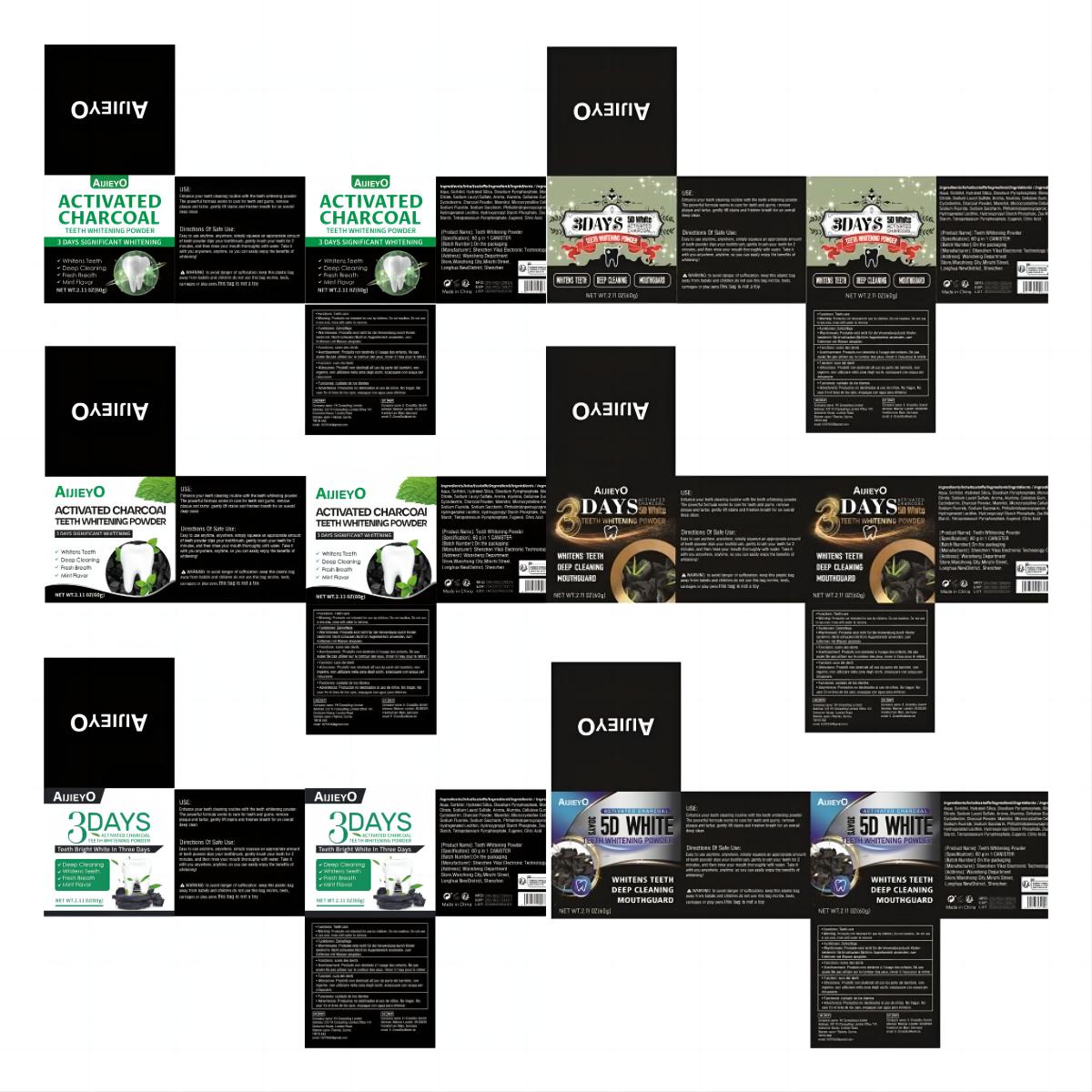 DRUG LABEL: Teeth Whitening Powder
NDC: 83809-023 | Form: POWDER
Manufacturer: Shenzhen Yikai Electronic Technology Co., Ltd.
Category: otc | Type: HUMAN OTC DRUG LABEL
Date: 20240626

ACTIVE INGREDIENTS: ACTIVATED CHARCOAL 10.94 g/100 g
INACTIVE INGREDIENTS: ALUMINUM OXIDE; STARCH, CORN; HYDRATED SILICA; CITRIC ACID MONOHYDRATE; EUGENOL; MONOSODIUM CITRATE; PHTHALIMIDOPEROXYCAPROIC ACID; SORBITOL; MANNITOL; TRIBASIC CALCIUM PHOSPHATE; HYDROGENATED SOYBEAN LECITHIN; CYCLODEXTRINS; CELLULOSE, MICROCRYSTALLINE; WATER; SODIUM LAURYL SULFATE; HYDROXYPROPYL CORN STARCH (5% SUBSTITUTION BY WEIGHT); POTASSIUM PYROPHOSPHATE; SODIUM ACID PYROPHOSPHATE; CARBOXYMETHYLCELLULOSE SODIUM, UNSPECIFIED FORM; SACCHARIN SODIUM

83809-023 Update V2.

Active Ingredient

Charcoal Powder 10.94%

Purpose

Teeth Whitening

Use

Enhance your teeth cleaning routine with the teeth whitening powder .

The powerful formula works to care for teeth and gums, remove plaque and tartar, gently lift stains and freshen breath for an overall
deep clean.

Warnings

Warnings: to avoid danger of suffocation.keep this plastic bag away from babies andchildren.do not use this bag incribs, beds carriages or play pens. this bag is not a toy.

Stop Use

Do not use:

● on irritated skin or on any area that is infected or reddenedon moles, birthmarks, warts with hair growing from them, warts on the face or mucous membranes

Keep Oot Of Reach Of Children

Directions

Easy to use anytime, anywhere, simply squeeze an appropriate amount of teeth powder dips your toothbrush, gently brush your teeth for 2 minutes, and then rinse your mouth thoroughly with water. Take it with you anywhere, anytime, so you can easily enjoy the benefits of whitening!

Inactive ingredients

Aqua, Sorbitol, Hydrated Silica, Disodium Pyrophosphate, Monosodium Citrate, Sodium Lauryl Sulfate, Aroma, Alumina, Cellulose Gum, Cyclodextrin, Mannitol, Microcrystalline Cellulose, Sodium Saccharin, Phthalimidoperoxycaproic Acid, Hydrogenated Lecithin, Hydroxypropyl Starch Phosphate, Zea Mays Starch, Tetrapotassium Pyrophosphate, Hydroxyapatite, Eugenol, Citric Acid.